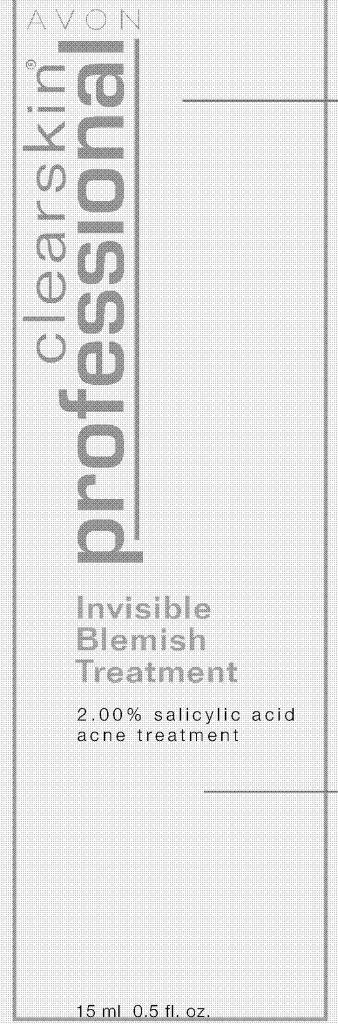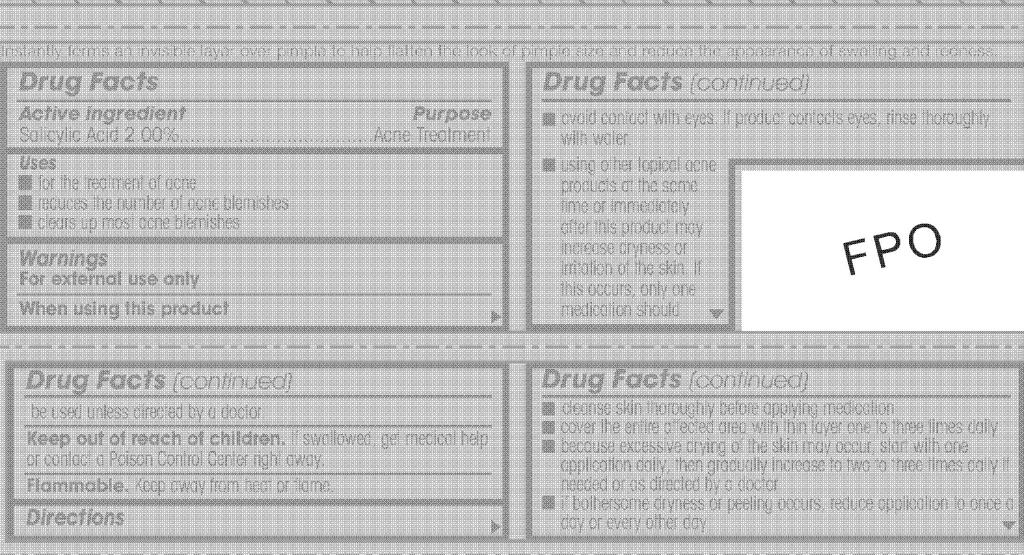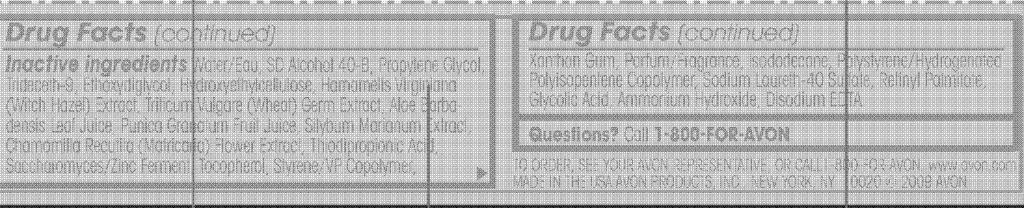 DRUG LABEL: CLEARSKIN PROFESSIONAL 
NDC: 10096-0180 | Form: GEL
Manufacturer: Avon Products, Inc.
Category: otc | Type: HUMAN OTC DRUG LABEL
Date: 20091210

ACTIVE INGREDIENTS: Salicylic Acid 0.30 mL/15 mL
INACTIVE INGREDIENTS: WATER; PROPYLENE GLYCOL; XANTHAN GUM; ISODODECANE; GLYCOLIC ACID

Drug Facts

Active ingredient Purpose

Salicylic Acid 2.00%....................................Acne Treatment

Uses

- for the treatment of acne
- reduces the number of acne blemishes
- clears up most acne blemishes

Warnings
For external use only

When using this product

- avoid contact with eyes. If product contacts eyes, rinse thoroughly with water.
- using other topical acne products at the same time or immediately after this product may increase dryness or irritation of the skin. If this occurs, only one medication should be used unless directed by a doctor

Keep out of reach of children. If swallowed, get medical help
or contact a Poison Control Center right away.

Flammable

Flammable. Keep away from heat or flame.

Directions

- cleanse skin thoroughly before applying medication
- cover the entire affected area with thin layer one to three times daily
- because excessive drying of the skin may occur, start with one application daily, then gradually increase to two to three times daily if needed or as directed by a doctor
- if bothersome dryness or peeling occurs, reduce application to once aday or every other day

INACTIVE INGREDIENT

Inactive ingredients Water/Eau, SD Alcohol 40-B, Propylene Glycol,
Trideceth-9, Ethoxydiglycol, Hydroxyethylcellulose, Hamamelis Virginiana
(Witch Hazel) Extract, Triticum Vulgare (Wheat) Germ Extract, Aloe Barbadensis
Leaf Juice, Punica Granatum Fruit Juice, Silybum Marianum Extract,
Chamomilla Recutita (Matricaria) Flower Extract, Thiodipropionic Acid,
Saccharomyces/Zinc Ferment, Tocopherol, Styrene/VP Copolymer,
Xanthan Gum, Parfum/Fragrance, Isododecane, Polystyrene/Hydrogenated
Polyisopentene Copolymer, Sodium Laureth-40 Sulfate, Retinyl Palmitate,
Glycolic Acid, Ammonium Hydroxide, Disodium EDTA.

Questions? Call 1-800-FOR-AVON